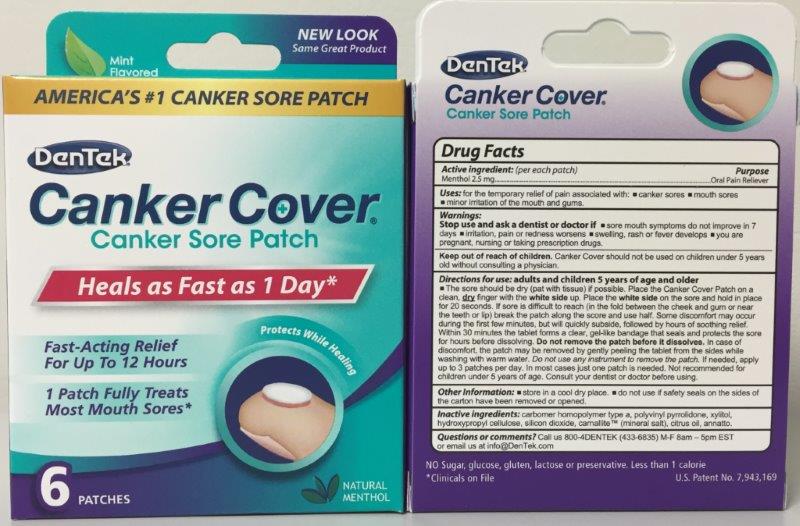 DRUG LABEL: Dentek Canker Cover
NDC: 10564-0910 | Form: PATCH, EXTENDED RELEASE
Manufacturer: Bershtel Enterprises
Category: otc | Type: HUMAN OTC DRUG LABEL
Date: 20251231

ACTIVE INGREDIENTS: MENTHOL 2.5 mg/194.85 1
INACTIVE INGREDIENTS: CITRUS MEDICA FRUIT; CARBOMER 934; POVIDONE; HYDROXYPROPYL CELLULOSE (TYPE E); SEA SALT; XYLITOL; MAGNESIUM STEARATE

Active Ingredient

menthol: 2.5 mg

Keep Out of Reach of Children Section

Warning: Keep out of reach of children.

Purpose Section

For Relief of pain associated with: canker sores & mouth sores.

Ask Doctor

Consult your dentist or doctor before using.

Indications & Usage

Adult and Children 5 year of age and older.

The sore should be dry (pat with tissue) is possible. Place the Canker Cover Patch on a clean, dry finger with the white side up. Place the white side on the sore and hold in place for 20 seconds. Within 30 minutes the tablet forms a clear, gel-like bandage that seals and protects the sore for hours before disolving. DO NOT REMOVE PATCH BEFORE IT DISSOLVES.

Dosage & Administration

2.5 mg per patch

Questions section

Call us 800-4Dentek (433-6835) M-F 8am - 5am EST or email us at Info@Dentek.com

Warning Section

Keep out of reach of children. If irritation, pain, or redness worsens, if swelling, rash or fever develops, or if sore mouth systoms persists for 7 days, see your doctor or dentist.

Inactive Ingredients

1. citrus medica fruit
2. povidone
3. colloidal silicon dioxide
4. carbomer 934
5. Xylitol
6. Hydroxypropyl
7. sea salt
8. magnesium stearate